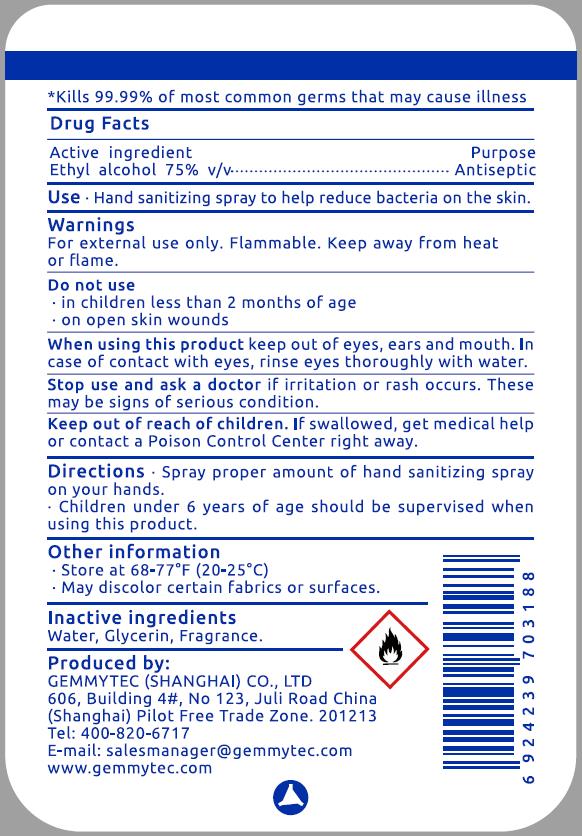 DRUG LABEL: Hand Sanitizing Sprays
NDC: 81343-122 | Form: LIQUID
Manufacturer: Gemmytec (Shanghai) Co., Ltd
Category: otc | Type: HUMAN OTC DRUG LABEL
Date: 20201229

ACTIVE INGREDIENTS: ALCOHOL 28.5 mL/38 mL
INACTIVE INGREDIENTS: GLYCERIN; WATER; LEMON OIL

Gemmytec EA 75% LIQ 38mL

Active Ingredient(s)

Ethyl alcohol 75% v/v. Purpose: Antiseptic

Purpose

Antiseptic

Use

Hand sanitizing spray to help reduce bacteria on the skin.

Warnings

For external use only. Flammable. Keep away from heat or flame.

Do not use

- in children less than 2 months of age
- on open skin wounds

When using this product keep out of eyes, ears and mouth. If case of contact with eyes, rinse eyes thoroughly with water.

Stop use and ask a doctor if irritation or rash occurs. These may be signs of serious condition.

Keep out of reach of children. If swallowed, get medical help or contact a Poison Control Center right away.

Directions

- Spray proper amount of hand sanitizing spray on your hands.
- Children under 6 years of age should be supervised when using this product.

Other information

- Store at 68-77℉ (20-25℃).
- May discolor certain fabrics or surfaces.

Inactive ingredients

Water, Glycerin, Fragrance.